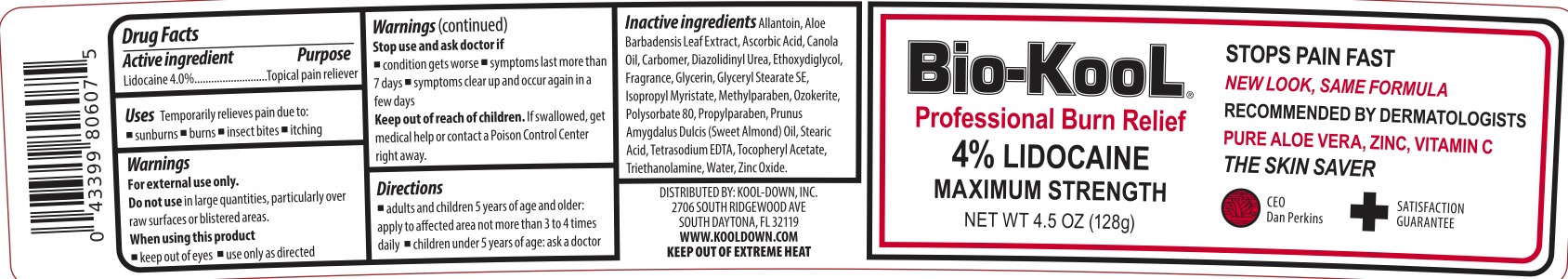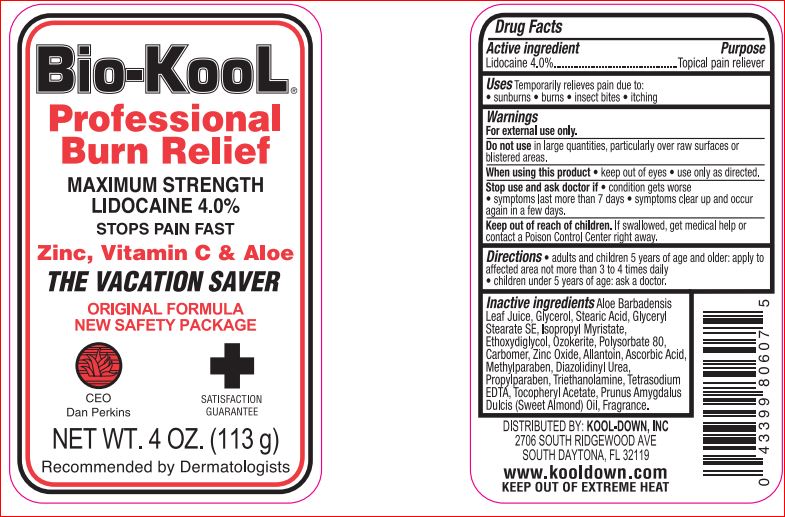 DRUG LABEL: Burn Relief Professional
NDC: 61566-201 | Form: CREAM
Manufacturer: Kool-Down Inc.
Category: otc | Type: HUMAN OTC DRUG LABEL
Date: 20250627

ACTIVE INGREDIENTS: LIDOCAINE 4 g/100 g
INACTIVE INGREDIENTS: ALOE; GLYCERIN; STEARIC ACID; GLYCERYL STEARATE SE; ISOPROPYL MYRISTATE; DIETHYLENE GLYCOL MONOETHYL ETHER; CERESIN; POLYSORBATE 80; CARBOXYPOLYMETHYLENE; ZINC OXIDE; ALLANTOIN; ASCORBIC ACID; METHYLPARABEN; DIAZOLIDINYL UREA; PROPYLPARABEN; TROLAMINE; EDETATE SODIUM; .ALPHA.-TOCOPHEROL ACETATE; ALMOND OIL

Drug Facts

ACTIVE INGREDIENT

Lidocaine - 4.0%

PURPOSE

Topical Pain Reliever

Uses

Temporarily relieves pain due to: sunburns, burns, insect bites, and itching.

WARNINGS

For external use only.

Do not use in large quantities, particularity over raw surfaces or blistered areas

When using this product keep out of eyes, use only as directed

Stop use and ask a doctor if condition worsens or symptoms last more than 7 days or clear up and occur again within a few days.

KEEP OUT OF REACH OF CHILDREN

Keep out of reach of the children. If swallowed, get medical help or contact a Poison Control Center right away.

DOSAGE AND ADMINISTRATION

Adults and children 5 years of age and older: apply to affected area, not more than 3-4 times daily. Children under 5 years of age: ask a doctor.

INACTIVE INGREDIENT

Aloe Barbadensis Leaf Juice, Glycerol, Stearic Acid, Glyceryl Stearate SE, Isopropyl Myristate, Ethoxydiglycol, Ozokerite, Polysorbate 80, Carbomer, Zinc Oxide, Allantoin, Ascorbic Acid, Methylparaben, Diazolidinyl Urea, Propylparaben, Triethanolamine, Tetrasodium EDTA, Tocopheryl Acetate, Prunus Amygdalus Dulcis (Sweet Almond) Oil, Fragrance.